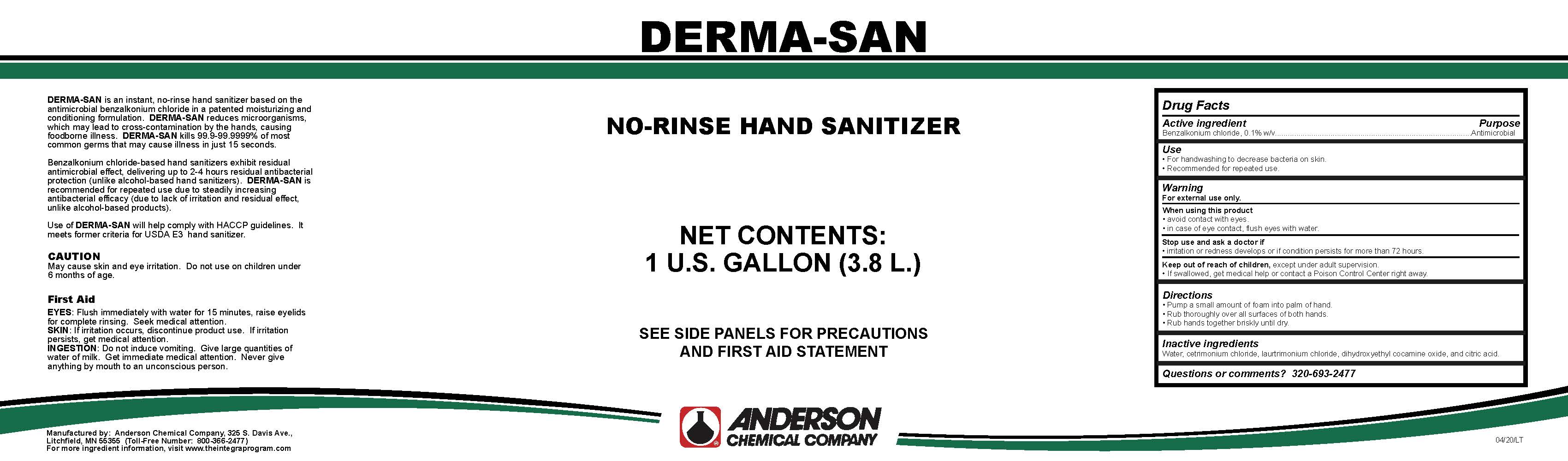 DRUG LABEL: Derma-San
NDC: 63131-0006 | Form: LIQUID
Manufacturer: Anderson Chemical Company
Category: otc | Type: HUMAN OTC DRUG LABEL
Date: 20200501

ACTIVE INGREDIENTS: BENZALKONIUM CHLORIDE 1 mg/1 mL
INACTIVE INGREDIENTS: CETRIMONIUM CHLORIDE; DIHYDROXYETHYL COCAMINE OXIDE; LAURTRIMONIUM CHLORIDE

Active ingredient

Benzalkonium Chlorine, 0.1% w/v

Purpose

Antimicrobial

Use

- For handwashing to decrease bacteria on skin
- Recommended for repeated use

Warning

For external use only

When using this product

- avoid contact with eyes.
- in case on eye contact, flush eyes with water

Use

- For handwashing to decrease bacteria on skin.
- Recommended for repeated use.

Stop use and ask a doctor if

- irritation or redness develops or if condition persists for more than 72 hours.

Keep out of reach of children.

- If swallowed, get medical help or contact a Poison Control Center right away.

Directions

- Pump a small amounts of foam into palm of hand.
- Rub thoroughly over all surfaces of both hands.
- Rub hands together briskly until dry.

Inactive ingredients

Water, cetrimonium chloride, laurtrimonium chloride, dihydroxyethyl cocamine oxide, and citric acid.

Questions or comment?

320-693-2477

Principal Display Panel

Derma-San

NO-RINSE HAND SANITIZER

NET CONTENTS: 1 US GALLON